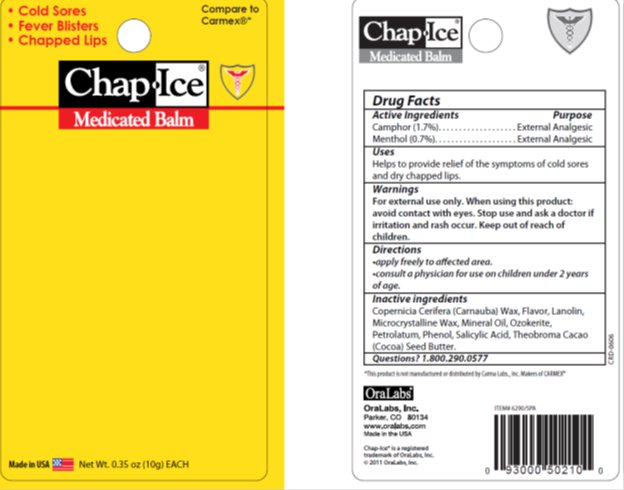 DRUG LABEL: ChapIce Medicated Balm
NDC: 63645-161 | Form: GEL
Manufacturer: OraLabs
Category: otc | Type: HUMAN OTC DRUG LABEL
Date: 20130801

ACTIVE INGREDIENTS: CAMPHOR (SYNTHETIC) 1.700 mg/1 g; MENTHOL 0.700 mg/1 g
INACTIVE INGREDIENTS: LIGHT MINERAL OIL 1.053 mg/1 g; PHENOL 0.400 mg/1 g; EUCALYPTUS OIL 0.500 mg/1 g; PETROLATUM 83.947 mg/1 g; CERESIN 1.000 mg/1 g; LANOLIN 8.000 mg/1 g

Drug Facts

Active ingredient

Camphor (1.7%), Menthol (0.7%)

Purpose

External Analgesic, External Analgesic

Keep Out of Reach of Children

If swallowed get medical help or contact a Poison Control Center right away.

Uses

Helps to provide relief of the symptoms of cold sores and dry chapped lips.

Warnings

For external use only. When using this product: avoid contact with eyes. Stop use and ask a doctor if irritation and rash occur.

Directions

Apply freely to affected area. Consult a physician for use on children under 2 years of age.

Inactive Ingredients

Copernicia Cerifera (Carnauba) Wax, Flavor, Lanolin, Microcrystalline Wax, Mineral Oil, Ozokerite, Petrolatum, Phenol, Salicylic Acid, Theobroma Cacao (Cocoa) Seed Butter.